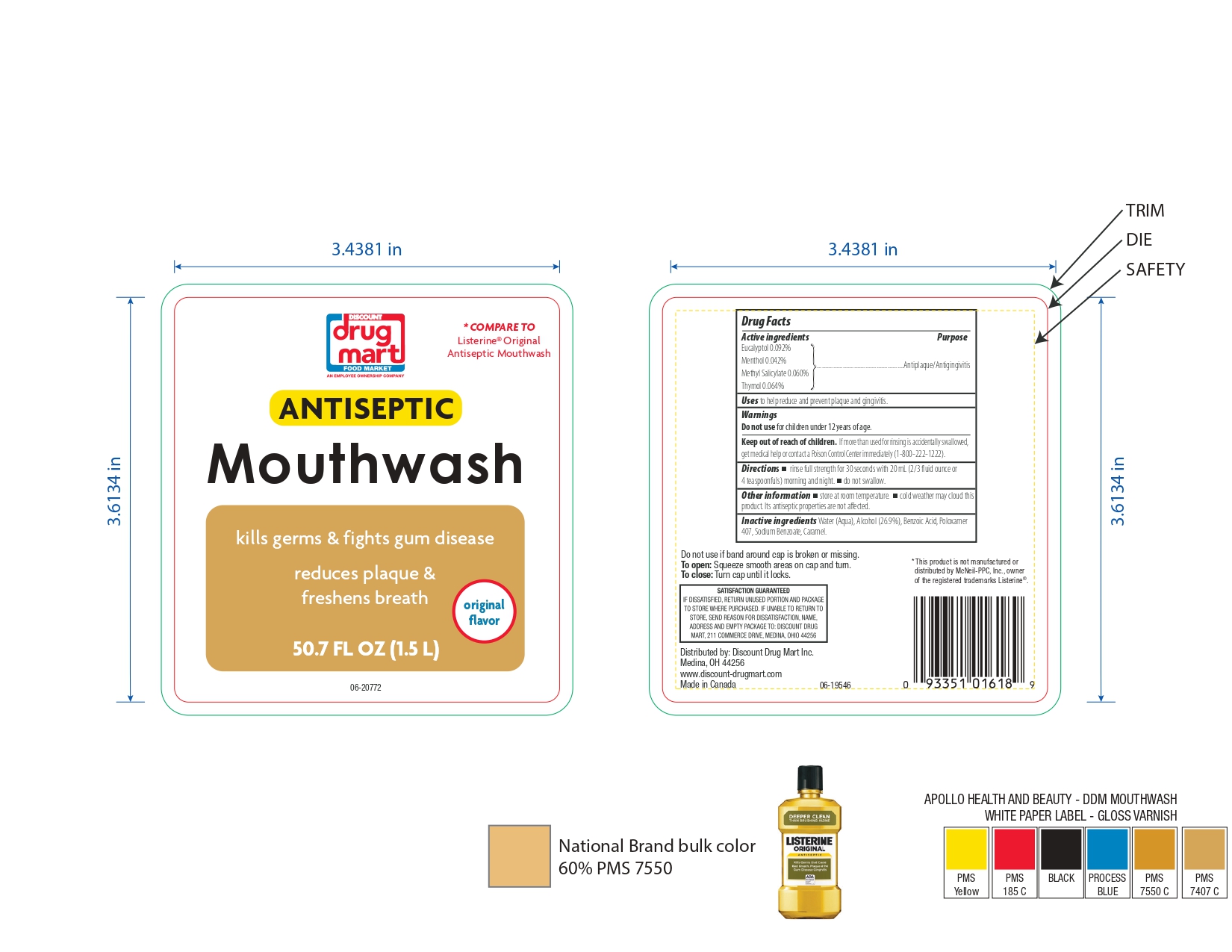 DRUG LABEL: Mouthwash
NDC: 53943-514 | Form: LIQUID
Manufacturer: DISCOUNT DRUG MART
Category: otc | Type: HUMAN OTC DRUG LABEL
Date: 20241020

ACTIVE INGREDIENTS: METHYL SALICYLATE 0.6 mg/1 mL; MENTHOL 0.42 mg/1 mL; THYMOL 0.64 mg/1 mL; EUCALYPTOL 0.92 mg/1 mL
INACTIVE INGREDIENTS: CARAMEL; ALCOHOL; POLOXAMER 407; WATER; BENZOIC ACID; SODIUM BENZOATE

53943-514-50 Antiseptic Mouthwash

Active Ingredients

Eucalyptol 0.092%
Menthol 0.042%
Methyl Salicylate 0.060%
Thymol 0.064%

Purpose

Antiplaque/Antigingivitis

Uses

to help reduce and prevent plaque and gingivitis.

Warnings

Do not use for children under 12 years of age.

Keep out of reach of children

If more than used for rinsing is accidentally swallowed, get medical help or contact a Poison Control Center immediately (1-800-222-1222).

Directions

- rinse full strength for 30 seconds with 20 mL (2/3 fluid ounce or 4 teaspoonfuls) morning and night.
- Do not swallow.

Other Information

- store at room temperature.
- cold weather may cloud this product. Its antiseptic properties are not affected.

Inactive Ingreduebts

Water (Aqua), Alcohol (26.9%), Benzoic Acid, Poloxamer 407, Sodium Benzoate, Caramel.